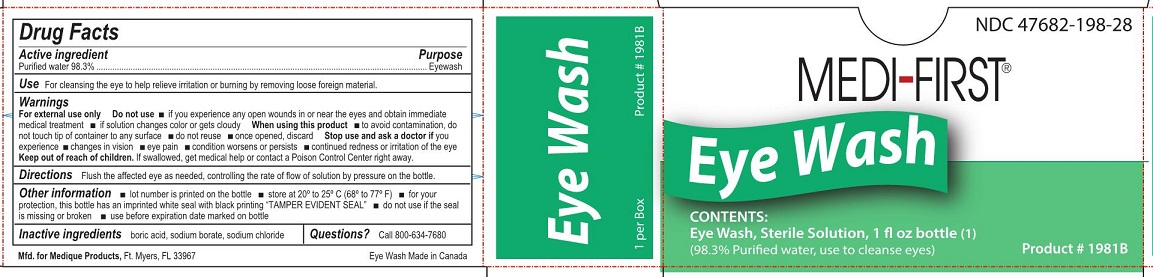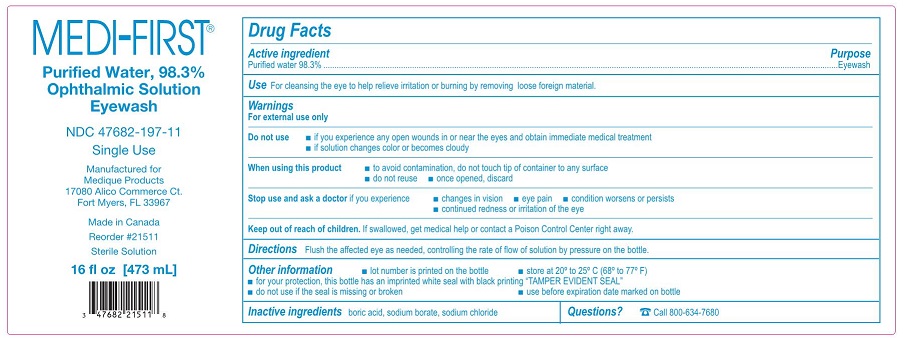 DRUG LABEL: Medi-First First Aid Eye Wash
NDC: 47682-198 | Form: SOLUTION
Manufacturer: Unifirst First Aid Corporation
Category: otc | Type: HUMAN OTC DRUG LABEL
Date: 20250908

ACTIVE INGREDIENTS: WATER 983 mg/1 mL
INACTIVE INGREDIENTS: BORIC ACID; SODIUM BORATE; SODIUM CHLORIDE

Medi-Wash Eyewash

Drug Facts

Active ingredient

Purified water 98.3%

Purpose

Eyewash

Use

For cleansing the eye to help relieve irritation or burning by removing loose foreign materia.

Warnings

For external use only

Do not use

- if you experience any open wounds in or near the eyes and obtain immediare medical treatment
- if solution changes color or becomes cloudy

When using this product

- to avoid contamination, do not touch tip of container to any surface
- do not reuse
- once opened, discard

Stop use and ask a doctor if you experience

- changes in vision
- eye pain
- condition worsens or persists
- continued redness or irritation of the eye

Keep out of reach of children.

If swallowed, get medical help or contact a Poison Control Center right away.

Directions

Flush the affected eye as needed, controlling the rate of flow of solution by pressure on the bottle.

.

Other information

- lot number is printed on the bottle
- store at 20º to 25º C [68º to 77º F]
- for your protection, this bottle has an imprinted white seal with black printing “TAMPER EVIDENT SEAL”
- do not use if this seal is missing or broken
- use before expiration date marked on bottle

Inactive ingredients

boric acid, sodium borate, sodium chloride

Questions?

Call 800-634-7680

Medi-First Eye Wash Label

Medi-First®

Purified Water, 98.3%

Ophthalmic Solution

Eyewash

NDC 47682-197-11

Single Use

Manufactured for

Medique Products

17080 Alico Commerce Ct.

Fort Myers, FL 33967

Made in Canada

Reorder #21511

Sterile Solution

16 fl oz [473 mL]

Medi-First Eyewash Label

NDC 47682-198-28

Medi-First®

Eyewash

Sterile Solution

1 fl oz bottle (1)

(98.3% Purified water, use to cleanse eyes)

Reorder #1981B